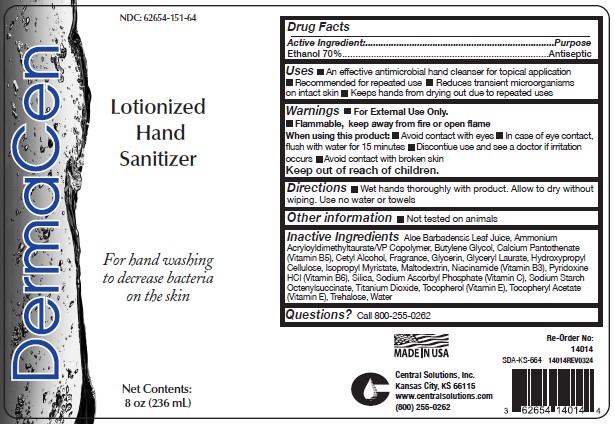 DRUG LABEL: DermaCen Lotionized Hand Sanitizer
NDC: 62654-151 | Form: LIQUID
Manufacturer: Central Solutions Inc
Category: otc | Type: HUMAN OTC DRUG LABEL
Date: 20240807

ACTIVE INGREDIENTS: ALCOHOL 70 mL/100 mL
INACTIVE INGREDIENTS: .ALPHA.-TOCOPHEROL ACETATE; TITANIUM DIOXIDE; TOCOPHEROL; BUTYLENE GLYCOL; CETYL ALCOHOL; PYRIDOXINE HYDROCHLORIDE; AMMONIUM ACRYLOYLDIMETHYLTAURATE/VP COPOLYMER; CALCIUM PANTOTHENATE; OCTENYLSUCCINIC ACID; MALTODEXTRIN; SILICON DIOXIDE; ALOE VERA LEAF; WATER; TREHALOSE; HYDROXYPROPYL CELLULOSE, UNSPECIFIED; ISOPROPYL MYRISTATE; GLYCERIN; GLYCERYL LAURATE; NIACINAMIDE; SODIUM ASCORBYL PHOSPHATE

Drug Facts 62654-151

Active Ingredient

Ethanol 70%

Purpose

Antiseptic

Uses

- An effective antimicrobial hand cleanser for topical application
- Recommended for repeated use
- Reduces transient microorganisms on intact skin
- Keeps hands from drying out due to repeated uses

Warnings

- For External Use Only.
- Flammable, keep away from fire or open flame

When using this product:

- Avoid contact with eyes
- In case of eye contact, flush with water for 15 nibutes
- Discontinue use and see a doctor if irritation occurs
- Avoid contact with broken skin

Directions

- Wet hands thoroughly with product. Allow to dry without wiping. Use no water or towels

Other information

- Not tested on animals

Inactive Ingredients

Aloe Barbadensis Leaf Juice, Ammonium Acryloyldimethyltaurate/VP Copolymer, Butylene Glycol, Calcium Pantothenate (Vitamin B5), Cetyl Alcohol, Fragrance, Glycerin, Glyceryl Laurate, Hydroxypropyl Cellulose, Isopropyl Myristate, Maltodextrin, Niacinamide (Vitamin B3), Pyridoxine HCl (Vitamin B6), Silica, Sodium Ascorbyl Phosphate (Vitamin C),Sodium Starch Octenylsuccinate, Titanium Dioxide, Tocopherol (Vitamin E), Tocopheryl Acetate (Vitamin E), Trehalose, Water

Questions?

Call 800-255-0262

PACKAGE LABEL

NDC: 62654-151-64

DermaCen

Lotionized

Hand

Sanitizer

For hand washing

to decrease bacteria

on the skin

Net Contents:

8 oz (236mL)